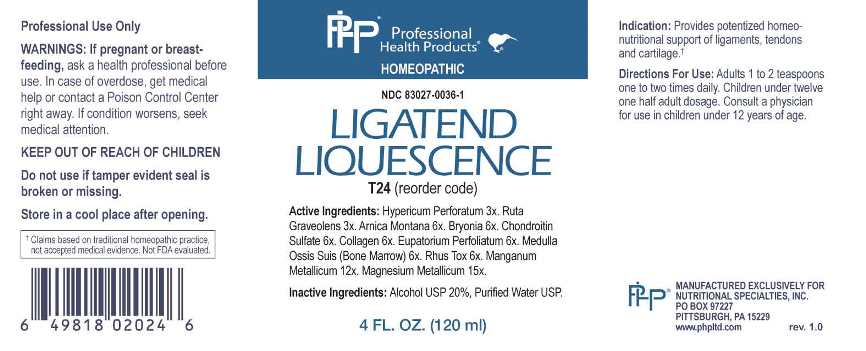 DRUG LABEL: Ligatend Liquescence
NDC: 83027-0036 | Form: LIQUID
Manufacturer: Nutritional Specialties, Inc.
Category: homeopathic | Type: HUMAN OTC DRUG LABEL
Date: 20250414

ACTIVE INGREDIENTS: HYPERICUM PERFORATUM WHOLE 3 [hp_X]/1 mL; RUTA GRAVEOLENS FLOWERING TOP 3 [hp_X]/1 mL; ARNICA MONTANA WHOLE 6 [hp_X]/1 mL; BRYONIA ALBA ROOT 6 [hp_X]/1 mL; CHONDROITIN SULFATE (BOVINE) 6 [hp_X]/1 mL; HYDROLYSED BOVINE COLLAGEN (ENZYMATIC; 3500 MW) 6 [hp_X]/1 mL; EUPATORIUM PERFOLIATUM FLOWERING TOP 6 [hp_X]/1 mL; SUS SCROFA BONE MARROW 6 [hp_X]/1 mL; TOXICODENDRON PUBESCENS LEAF 6 [hp_X]/1 mL; MANGANESE 12 [hp_X]/1 mL; MAGNESIUM 15 [hp_X]/1 mL
INACTIVE INGREDIENTS: WATER; ALCOHOL

DRUG FACTS:

ACTIVE INGREDIENTS:

Hypericum Perforatum 3X, Ruta Graveolens 3X, Arnica Montana 6X, Bryonia 6X, Chondroitin Sulfate 6X, Collagen 6X, Eupatorium Perfoliatum 6X, Medulla Ossis Suis (Bone Marrow) 6X, Rhus Tox 6X, Manganum Metallicum 12X, Magnesium Metallicum 15X.

PURPOSE:

Provides potentized homeo-nutritional support of ligaments, tendons and cartilage.†

†Claims based on traditional homeopathic practice, not accepted medical evidence. Not FDA evaluated.

WARNINGS:

Professional Use Only

If pregnant or breast-feeding, ask a health professional before use.

In case of overdose, get medical help or contact a Poison Control Center right away.

If condition worsens, seek medical attention.

KEEP OUT OF REACH OF CHILDREN

Do not use if tamper evident seal is broken or missing.

Store in a cool place after opening

KEEP OUT OF REACH OF CHILDREN:

In case of overdose, get medical help or contact a Poison Control Center right away.

DIRECTIONS:

Adults 1 to 2 teaspoons one to two times daily. Children under twelve one half adult dosage. Consult a physician for use in children under 12 years of age.

INDICATIONS:

Provides potentized homeo-nutritional support of ligaments, tendons and cartilage.†

†Claims based on traditional homeopathic practice, not accepted medical evidence. Not FDA evaluated.

INACTIVE INGREDIENTS:

Alcohol USP 20%, Purified Water USP.

QUESTIONS:

MANUFACTURED EXCLUSIVELY FOR

NUTRITIONAL SPECIALTIES, INC.

PO BOX 97227

PITTSBURG, PA 15229

www.phpltd.com

PACKAGE LABEL DISPLAY:

Professional

Health Products

HOMEOPATHIC

NDC 83027-0036-1

LIGATEND

LIQUESCENCE

4 FL. OZ (120 ml)